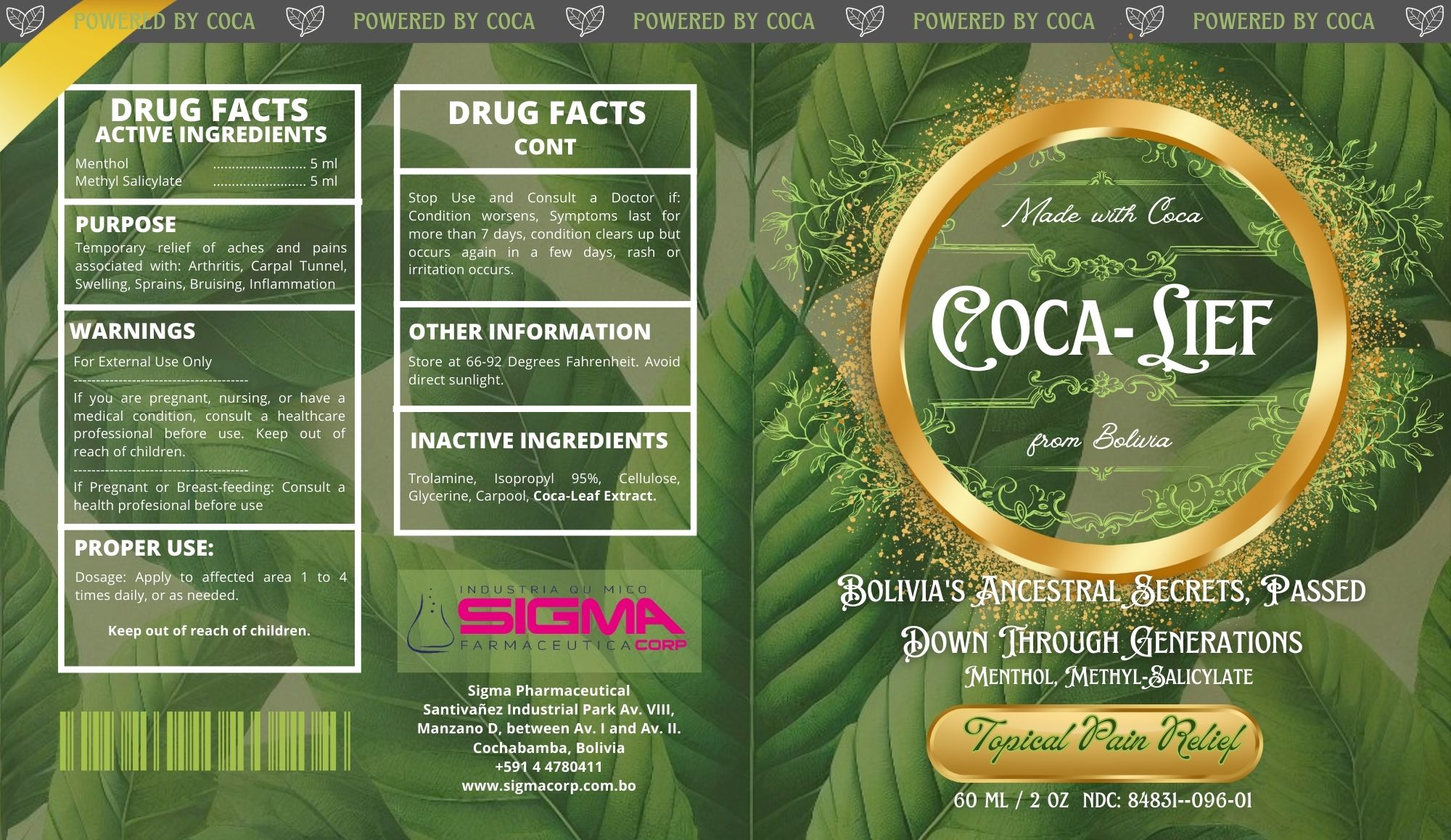 DRUG LABEL: COCA LIEF
NDC: 84831-096 | Form: GEL
Manufacturer: INDUSTRIA QUIMICO FARMACEUTICA SIGMA CORP. S.R.L.
Category: homeopathic | Type: HUMAN OTC DRUG LABEL
Date: 20250117

ACTIVE INGREDIENTS: METHYL SALICYLATE 12500 mg/100000 mg; MENTHOL 1500 mg/100000 mg
INACTIVE INGREDIENTS: GLYCERIN 401 mg/100000 mg; HYDROXYPROPYLCELLULOSE 800 mg/100000 mg; CARBOMER 940 1000 mg/100000 mg; ERYTHROXYLUM COCA LEAF 500 mg/100000 mg; WATER 60999 mg/100000 mg; METHYLPARABEN 100 mg/100000 mg; TROLAMINE 300 mg/100000 mg; ALCOHOL 95% 21900 mg/100000 mg

COCA LIEF

Active Ingredients

Menthol ........... 1.5 mg ..... Topical Analgesic
Methyl Salicylate 12.5 mg ..... Topical Analgesic

Purpose

Temporary relief of aches and pains associated with <Arthritis, Carpal Tunnel, Swelling, Sprains, Brusing and Inflamation

WARNINGS

ASK DOCTOR/PHARMACIST

If you are pregnant, nursing, or have a medical condition consult a healthcare professional before use.

INDICATIONS AND USAGE

For External Use Only

PREGNANCY OR BREAST FEEDING

If pregnant or breastfeeding consult a healthcare professional before use.

Keep out of reach of children.

Stop use and consult a doctor if condition worsens or if sympotoms last for more than 7 days, or if condition clears up but occurs again a few days later, or if you dicsover a rash/irritation.

OTHER SAFETY INFORMATION

Store at 66 to 92 degress Farenheit. Do not leave in direct sunlight.

DOSAGE AND ADMINISTRATION

aPPLY 3 TO 4 TIMES DAILY AS NEEDED

Inactive Ingredients

Trolamine, 95% Isopropyl Alcohol, cellulose, Gycerine, Coca-leaf extract.